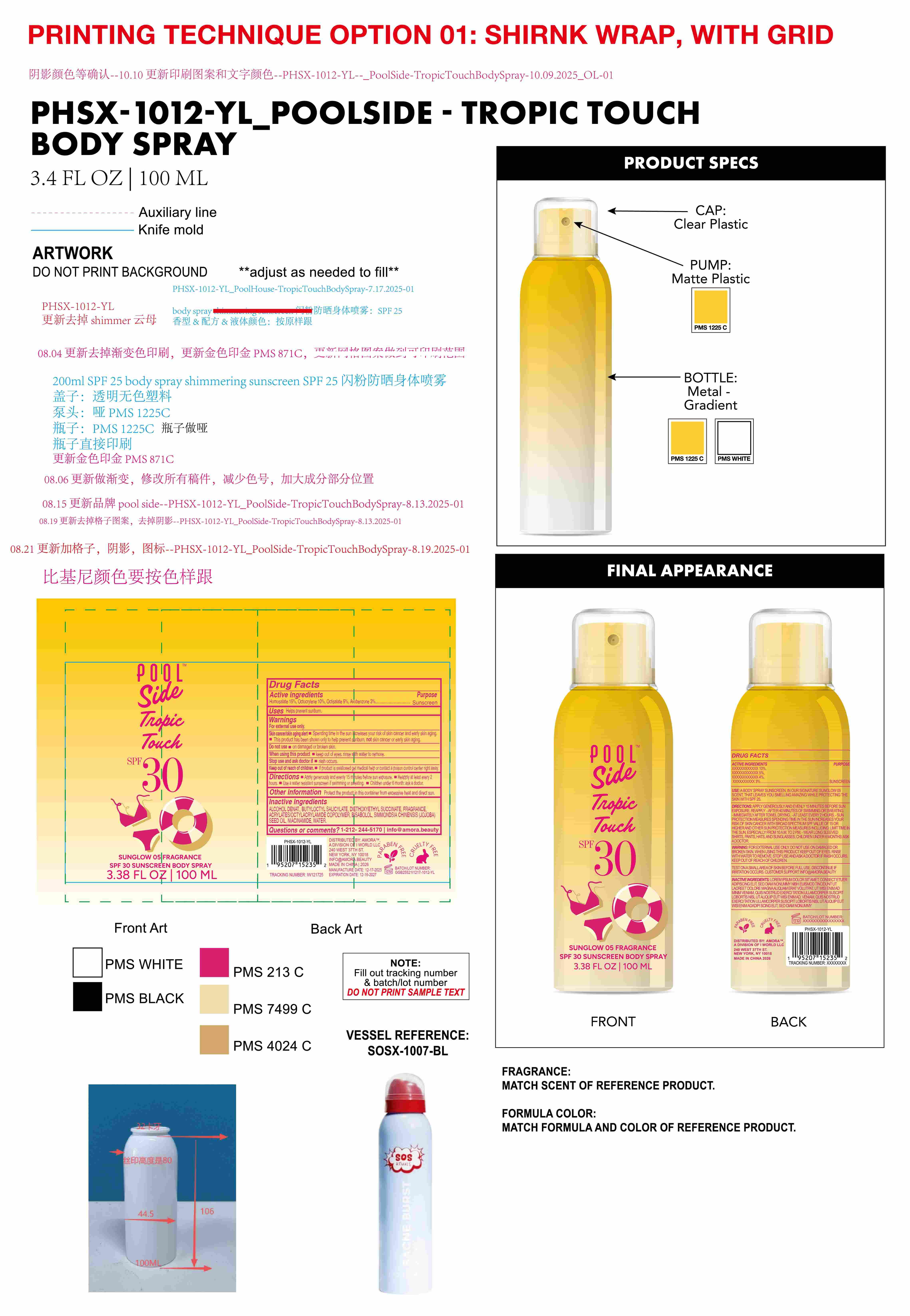 DRUG LABEL: Poolside Tropic Touch SPF 30 Sunscreen Body spray.
NDC: 85161-143 | Form: SPRAY
Manufacturer: Longway Technology(Guangzhou)Co.,Ltd.
Category: otc | Type: HUMAN OTC DRUG LABEL
Date: 20251203

ACTIVE INGREDIENTS: OCTOCRYLENE 0.1 g/1 mL; OCTISALATE 0.05 g/1 mL; HOMOSALATE 0.15 g/1 mL; AVOBENZONE 0.03 g/1 mL
INACTIVE INGREDIENTS: BISABOLOL; SIMMONDSIA CHINENSIS (JOJOBA) SEED OIL; ACRYLATES/OCTYLACRYLAMIDE COPOLYMER (40000 MW); BUTYLOCTYL SALICYLATE; WATER; NIACINAMIDE; DIETHOXYETHYL SUCCINATE; FRAGRANCE 13576; ALCOHOL

ACTIVE INGREDIENT

Homosalate 15%, Octocrylene 10%, Octisalate 5% , Avobenzone 3%

PURPOSE

Sunscreen

Keep out of reach of children.

lf product is swallowed get medical help or contact a poison control center right away.

INACTIVE INGREDIENT

ALCOHOL DENAT. , BUTYLOCTYL SALICYLATE, DIETHOXYETHYL SUCCINATE,FRAGRANCE, ACRYLATES/OCTYLACRYLAMIDE COPOLYMER, BISABOLOL, SIMMONDSIA CHINENSIS (JOJOBA)SEED OIL, NIACINAMIDE , WATER

OTHER SAFETY INFORMATION

Protect the product in this container from excessive heat and direct sun.

QUESTIONS

1-212-244-5170 | info@amora.beauty

WARNINGS

For external use only.

Skin cancer/skin aging alert

Spending time in the sun increases your risk of skin cancer and early skin aging.

This product has been shown only to help prevent sunburn, not skin cancer or early skin aging.

Do not use . on damaged or broken skin.

When using this product . keep out of eyes. rinse with water to remove.

Stop use and ask doctor if . rash occurs.

Keep out of reach of children.lf product is swallowed get medical help or contact a poison control center right away.

INDICATIONS AND USAGE

Helps prevent sunbumn.

Directions

Apply generously and evenly 15 minutes before sun exposure.

Reapply at least every 2hours..

Use a water resistant sunscreen if swimming or sweating.

Children under 6 month: ask a doctor.